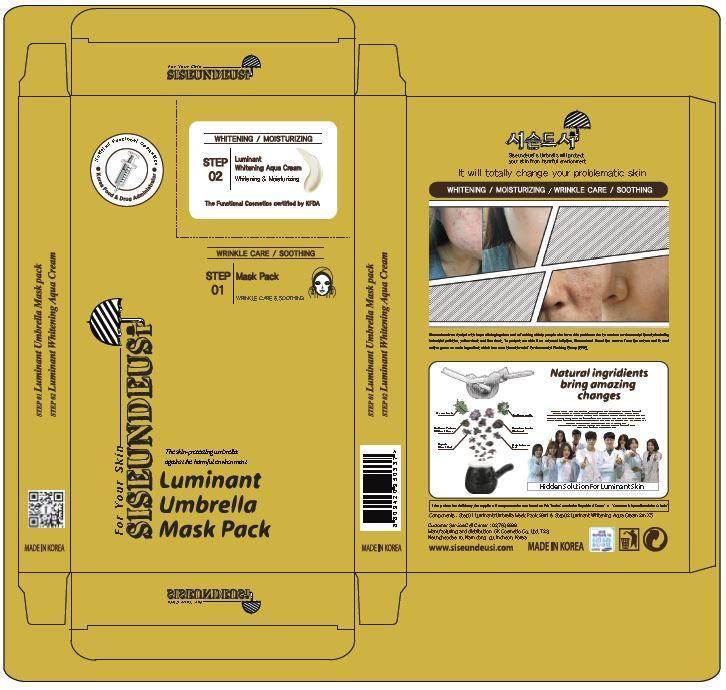 DRUG LABEL: LUMINANT UMBRELLA MASK PACK
NDC: 70098-0002 | Form: LIQUID
Manufacturer: GK COSMETIC CO., LTD.
Category: otc | Type: HUMAN OTC DRUG LABEL
Date: 20191206

ACTIVE INGREDIENTS: ALLANTOIN 0.1 g/100 mL
INACTIVE INGREDIENTS: BUTYLENE GLYCOL; GLYCERIN

Drug Facts

ACTIVE INGREDIENT

allantoin

INACTIVE INGREDIENT

glycerin, butylene glycol, etc.

PURPOSE

skin protectant

keep out of reach of the children

INDICATIONS AND USAGE

1. After wash your face, take our STEP01 Luminant Umbrella Facial Mask and put it on your face.

2. Take off the sheet after 15 to 20 minutes when it gets absorbed into your skin

3. Tap your skin softly for your skin to absorb anything left on the skin.

4. Put STEP02 Luminant Whitening Aqua Creme(2 ml) evenly on your face.

When we consider skin turn over period, using the productconsistently for

4 weeks is the most effective way to use the product.

WARNINGS

1. Do not use in the following cases(Eczema and scalp wounds)
2.Side Effects
1)Due to the use of this druf if rash, irritation, itching and symptopms of hypersnesitivity occur dicontinue use and consult your phamacisr or doctor
3.General Precautions
1)If in contact with the eyes, wash out thoroughty with water If the symptoms are servere, seek medical advice immediately
2)This product is for exeternal use only. Do not use for internal use
4.Storage and handling precautions
1)If possible, avoid direct sunlight and store in cool and area of low humidity
2)In order to maintain the quality of the product and avoid misuse
3)Avoid placing the product near fire and store out in reach of children

DOSAGE AND ADMINISTRATION

for external use only